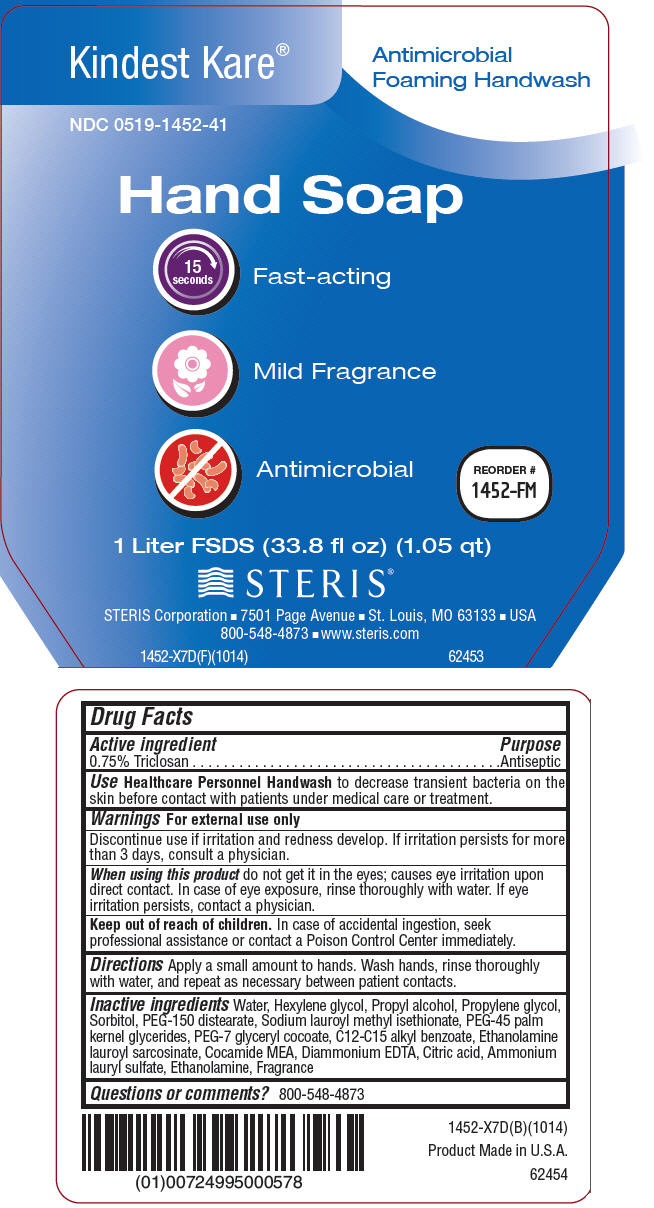 DRUG LABEL: Kindest Kare Antimicrobial Foaming Handwash 
NDC: 0519-1452 | Form: LIQUID
Manufacturer: STERIS Corporation
Category: otc | Type: HUMAN OTC DRUG LABEL
Date: 20141203

ACTIVE INGREDIENTS: Triclosan 0.75 g/100 mL
INACTIVE INGREDIENTS: water; Hexylene glycol; Propyl alcohol; Propylene glycol; Sorbitol; PEG-150 distearate; sodium lauroyl methyl isethionate; Peg-45 Palm Kernel Glycerides; PEG-7 glyceryl cocoate; Alkyl (C12-15) benzoate; Lauroyl sarcosine; Coco monoethanolamide; Edetic Acid; Citric acid monohydrate; Ammonium lauryl sulfate; Monoethanolamine

Kindest Kare® Antimicrobial Foaming Handwash
Healthcare Personnel Handwash

Drug Facts

Active ingredient

0.75% Triclosan

Purpose

Antiseptic

Use

Healthcare Personnel Handwash to decrease transient bacteria on the skin before contact with patients under medical care or treatment.

Warnings

For external use only

STOP USE

Discontinue use if irritation and redness develop. If irritation persists for more than 3 days, consult a physician.

When using this product do not get it in the eyes; causes eye irritation upon direct contact. In case of eye exposure, rinse thoroughly with water. If eye irritation persists, contact a physician.

Keep out of reach of children. In case of accidental ingestion, seek professional assistance or contact a Poison Control Center immediately.

Directions

Apply a small amount to hands. Wash hands, rinse thoroughly with water, and repeat as necessary between patient contacts.

Inactive ingredients

Water, Hexylene glycol, Propyl alcohol, Propylene glycol, Sorbitol, PEG-150 distearate, Sodium lauroyl methyl isethionate, PEG-45 palm kernel glycerides, PEG-7 glyceryl cocoate, C12-C15 alkyl benzoate, Ethanolamine lauroyl sarcosinate, Cocamide MEA, Diammonium EDTA, Citric acid, Ammonium lauryl sulfate, Ethanolamine, Fragrance

Questions or comments?

800-548-4873

PRINCIPAL DISPLAY PANEL - 1 Liter Bottle Label

Kindest Kare®

Antimicrobial
Foaming Handwash

NDC 0519-1452-41

Hand Soap

15
seconds
Fast-acting

Mild Fragrance

Antimicrobial

REORDER #
1452-FM

1 Liter FSDS (33.8 fl oz) (1.05 qt)

STERIS®

STERIS Corporation ◾ 7501 Page Avenue ◾ St. Louis, MO 63133 ◾ USA
800-548-4873 ◾ www.steris.com

1452-X7D(F)(1014)

62453